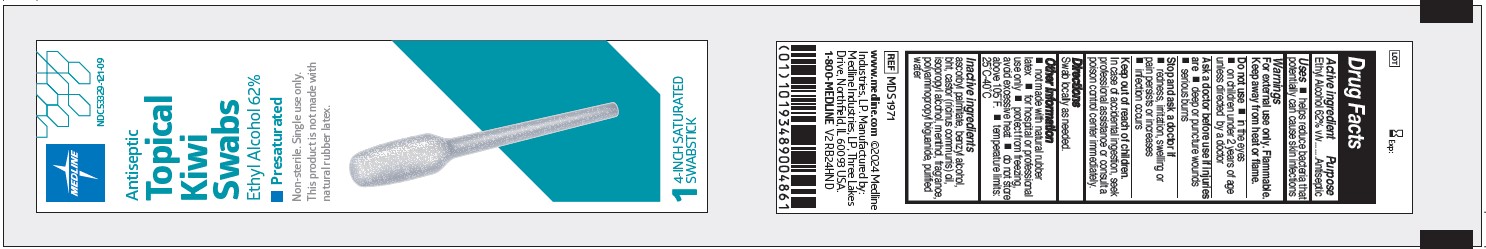 DRUG LABEL: Medline
NDC: 53329-121 | Form: SWAB
Manufacturer: Medline Industries, LP
Category: otc | Type: HUMAN OTC DRUG LABEL
Date: 20251106

ACTIVE INGREDIENTS: ALCOHOL 62 mL/100 mL
INACTIVE INGREDIENTS: ISOPROPYL ALCOHOL; ASCORBYL PALMITATE; WATER; BUTYLATED HYDROXYTOLUENE; MENTHOL; POLYAMINOPROPYL BIGUANIDE; BENZYL ALCOHOL; CASTOR OIL

121 Antiseptic Topical Kiwi Swabs Ethyl Alcohol 62%

Active ingredient

Ethyl Alcohol 62% v/v

Purpose

Antiseptic

Uses

- helps reduce bacteria that potentially can cause skin infections

Warnings

For external use only. Flammable. Keep away from heat or flame.

Do not use

- in the eyes
- on children under 2 years of age unless directed by a doctor

Ask a doctor before use if injuries are

- deep or puncture wounds
- serious burns

Stop and ask a doctor if

- redness, irritation, swelling or pain persists or increases
- infection occurs

Keep out of reach of children.

In case of accidental ingestion, seek professional assistance or consult a poison control center immediately.

Directions

Swab locally as needed.

Other information

- not made with natural rubber latex
- for hospital or professional use only
- protect from freezing, avoid excessive heat
- do not store above 105˚F.
- temperature limits: 25˚C-40˚C

Inactive ingredients

ascorbyl palmitate, benzyl alcohol, BHT, castor (ricinus communis) oil, fragrance, isopropyl alcohol, menthol, polyaminopropyl biguanide, purified water

Manufacturer Information

www.medline.com

©2024 Medline Industries, LP

Manufactured by: Medline Industries, LP,

Three Lakes Drive, Northfield, IL 60093 USA.

1-800-MEDLINE

REF: MDS1971